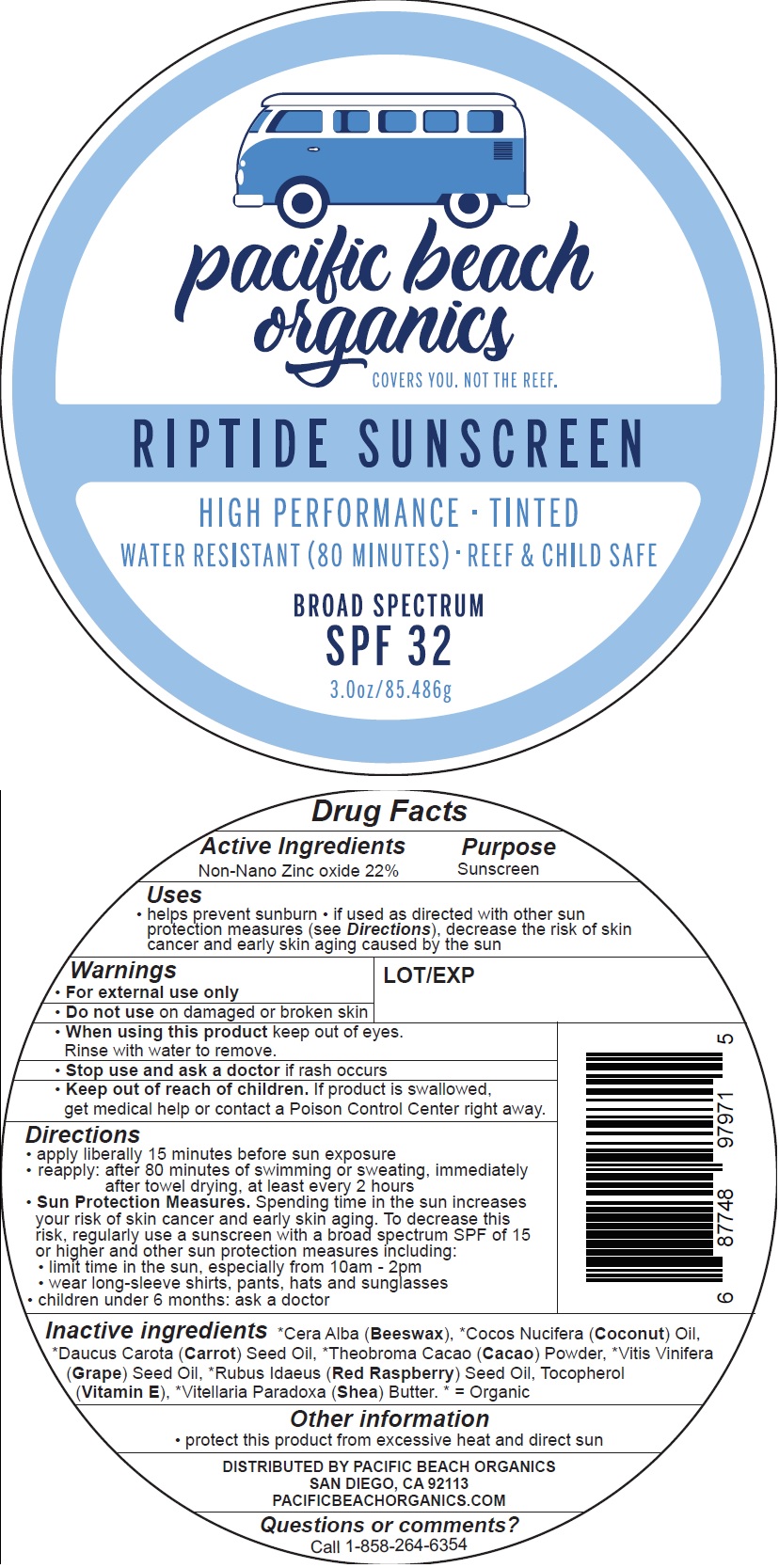 DRUG LABEL: Riptide Sunscreen Tinted
NDC: 73644-001 | Form: PASTE
Manufacturer: Pacific Beach Organics Co.
Category: otc | Type: HUMAN OTC DRUG LABEL
Date: 20200220

ACTIVE INGREDIENTS: ZINC OXIDE 220 mg/1 g
INACTIVE INGREDIENTS: WHITE WAX; COCONUT OIL; CARROT; COCOA; GRAPE SEED OIL; RASPBERRY; TOCOPHEROL; SHEA BUTTER

Riptide Sunscreen Tinted

Active Ingredients

Non-Nano Zinc oxide 22%

Purpose

Sunscreen

Uses

• helps prevent sunburn • if used as directed with other sun protection measures (see Directions), decrease the risk of skin cancer and early skin aging caused by the sun

Warnings

• For external use only

Do not use

- on damaged or broken skin

When using this product

- keep out of eyes. Rinse with water to remove.

Stop use and ask a doctor

- if rash occurs

Keep out of reach of children.

- If product is swallowed, get medical help or contact a Poison Control Center right away.

Directions

• apply liberally 15 minutes before sun exposure
• reapply: after 80 minutes of swimming or sweating, immediately after towel drying, at least every 2 hours
• Sun Protection Measures. Spending time in the sun increases your risk of skin cancer and early skin aging. To decrease this
risk, regularly use a sunscreen with a broad spectrum SPF of 15 or higher and other sun protection measures including:
• limit time in the sun, especially from 10am - 2pm
• wear long-sleeve shirts, pants, hats and sunglasses
• children under 6 months: ask a doctor

Inactive ingredients

*Cera Alba (Beeswax), *Cocos Nucifera (Coconut) Oil, *Daucus Carota (Carrot) Seed Oil, *Theobroma Cacao (Cacao) Powder, *Vitis Vinifera (Grape) Seed Oil, *Rubus Idaeus (Red Raspberry) Seed Oil, Tocopherol (Vitamin E), *Vitellaria Paradoxa (Shea) Butter. * = Organic

Other information

• protect this product from excessive heat and direct sun

DISTRIBUTED BY PACIFIC BEACH ORGANICS
SAN DIEGO, CA 92113
PACIFICBEACHORGANICS.COM

Questions or comments?

Call 1-858-264-6354